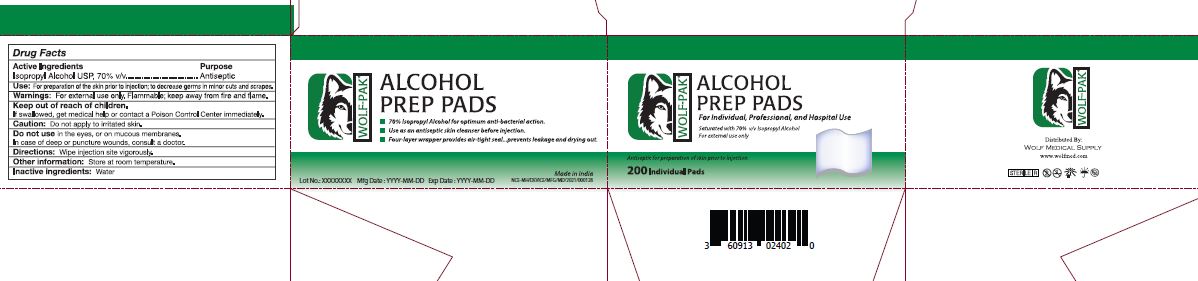 DRUG LABEL: Alcohol Prep Pads
NDC: 60913-024 | Form: SWAB
Manufacturer: Phoenix Healthcare Solutions LLC
Category: otc | Type: HUMAN OTC DRUG LABEL
Date: 20251023

ACTIVE INGREDIENTS: ISOPROPYL ALCOHOL 70 mL/100 mL
INACTIVE INGREDIENTS: WATER

Wolf Alcohol prep pad 200 ct

Active Ingredients

Isopropyl Alcohol 70% v/v

Purpose

Antiseptic

Use

For preparation of skin prior to injection, to decrease germs in minor cuts and scrapes

Warning

For external use only. Flammable. KEep away from Fire and Flame

Keep out of reach of children

If swallowed get Medical help or contact a poison control center immediately.

Caution

Do not apply to irritated skin.

Do not use in the eyes, or on mucus membranes. Incase of deep or puncture wounds, consult a doctor.

Directions

Wipe Injection site vigorously.

Other Information

Store at Room Temperature

Inactive Ingredient

Water